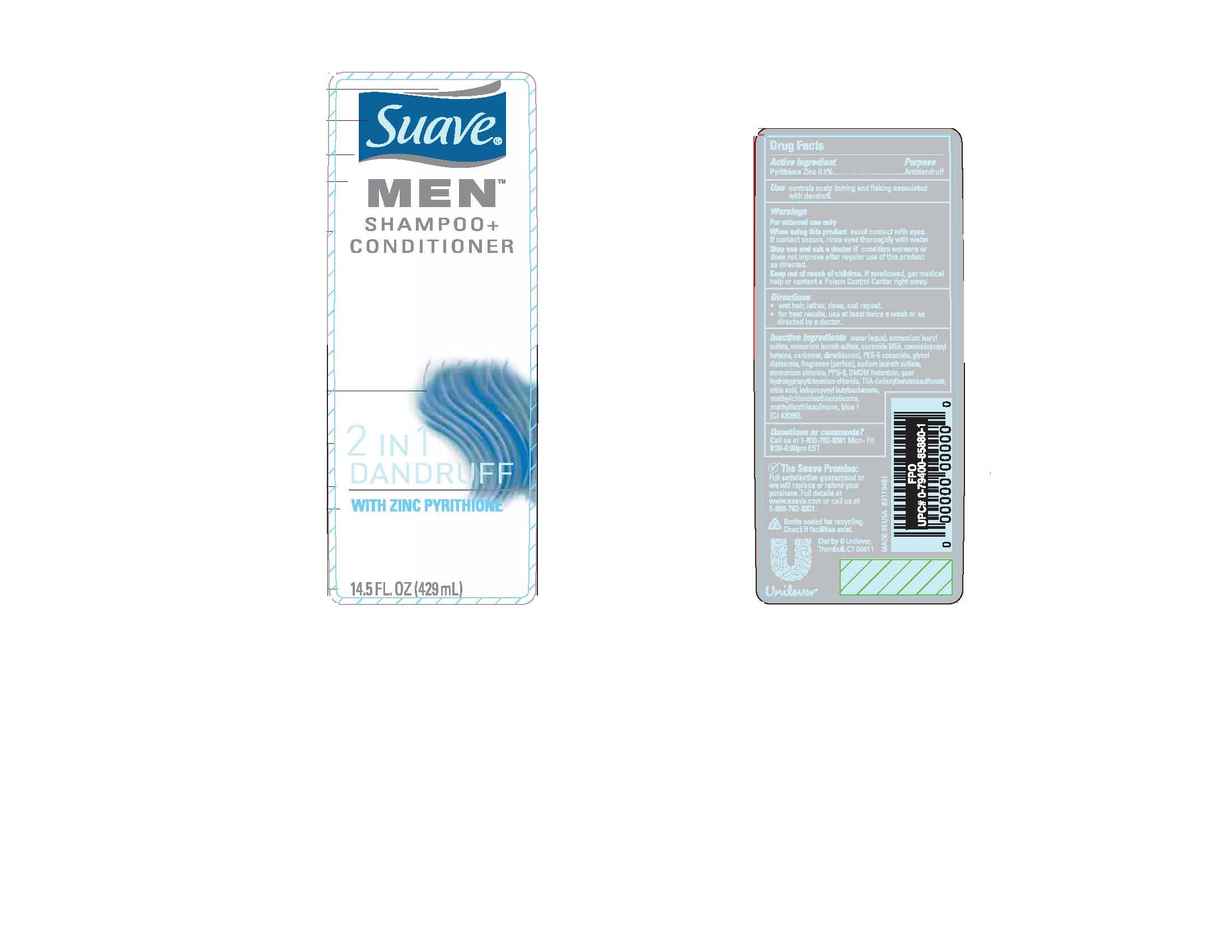 DRUG LABEL: Suave
NDC: 64942-1050 | Form: SHAMPOO
Manufacturer: Conopco Inc. d/b/a Unilever
Category: otc | Type: HUMAN OTC DRUG LABEL
Date: 20091015

ACTIVE INGREDIENTS: Pyrithione Zinc 0.5 mL/100 mL

Suave Men 2 in 1 Dandruff shampoo+conditioner PDP front and back and drug facts box

Active Ingredient Purpose

Pyrithione Zinc (0.5%)....Anti-dandruff

PURPOSE

Use controls scalp itching and flaking associated with dandruff.

WARNINGS

For external use only

When using this product avoid contact with eyes. If contact occurs, rinse eyes thoroughly with water.

Stop use and ask a doctor if condition worsens or does not improve after regular use of this product as directed.

Keep out of reach of children. If swallowed, get medical help or contact a Poison Control Center right away.

INACTIVE INGREDIENT

Water (Aqua), Ammonium Lauryl Sulfate, Ammonium Laureth Sulfate, Cocamide MEA, Cocamidopropyl Betaine, Carbomer, Dimethiconol, PEG-5 Cocamide, Glycol Distearate, Fragrance (Parfum), Sodium Laureth Sulfate, PPG-9, Ammonium Chloride, DMDM Hydantoin, Citric Acid, Guar Hydroxypropyltrimonium Chloride, TEA-Dodecylbenzenesulfonate, Iodopropynyl Butylcarbamate, Methylchloroisothiazolinone, Methylisothiazolinone, Blue 1 (CI 42090).

Questions/Comments?

call us at 1-800-782-8301 Mon - Fri 8:30 - 6:00 pm EST

PACKAGE LABEL

PDP 14.5 oz front and back